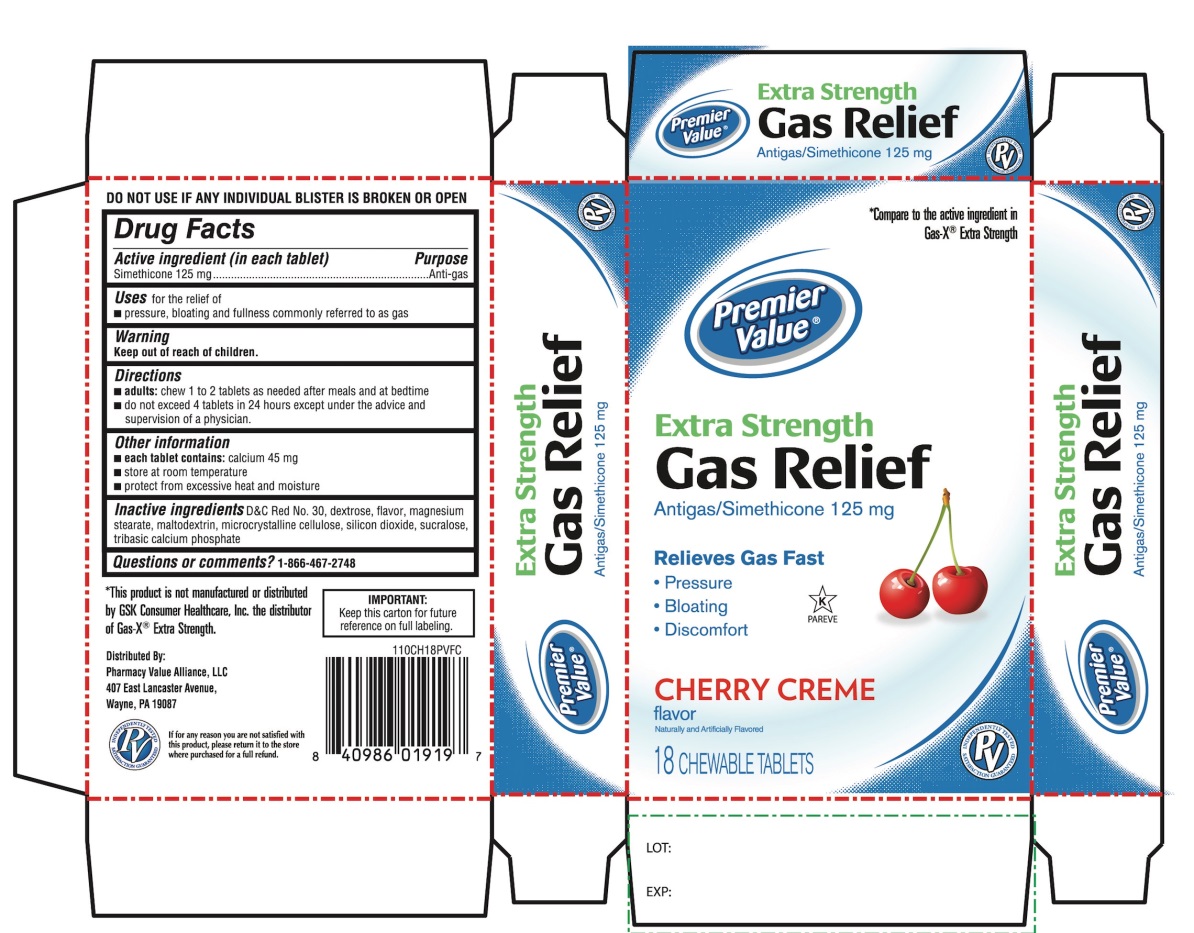 DRUG LABEL: Premier Value
NDC: 68016-811 | Form: TABLET, CHEWABLE
Manufacturer: PHARMACY VALUE ALLIANCE, LLC
Category: otc | Type: HUMAN OTC DRUG LABEL
Date: 20241028

ACTIVE INGREDIENTS: DIMETHICONE, UNSPECIFIED 125 mg/1 1
INACTIVE INGREDIENTS: D&C RED NO. 30; DEXTROSE, UNSPECIFIED FORM; MAGNESIUM STEARATE; MALTODEXTRIN; MICROCRYSTALLINE CELLULOSE; SILICON DIOXIDE; SUCRALOSE; TRIBASIC CALCIUM PHOSPHATE

Premier Value Extra Strength Gas Relief

Active ingredient (in each tablet)

Simethicone 125 mg

Purpose

Anti-gas

Uses

For the relief of

- Pressure, bloating and fullness commonly referred to as gas

Directions

- adults: chew 1 to 2 tablets as needed after meals and at bedtime.
- do not exceed 4 tablets in a 24 hours except under the advice and supervision of a physician.

Other information

- each tablets contains: calcium 45 mg
- store at room temperature
- protect from excessive heat and moisture

DO NOT USE IF ANY INDVIDUAL BLISTER IS BROKEN OR OPEN

Inactive ingredients

D&C Red No. 30, dextrose, flavor, magnesium stearate, maltodextrin, microcrystalline cellulose, silicon dioxide, sucralose, tribasic calcium phosphate.

Principal Display Panel

Premier Value®

NDC 68016-811-18

*Compare to the active ingredient in Gas-X® Extra Strength

Extra Strength

Gas Relief

Antigas/Simethicone 125 mg

Relieves:

- Pressure
- Bloating
- Discomfort

Cherry Creme Flavor

Naturally and Artificially Flavored

18 CHEWABLE TABLETS

K PAREVE

*This product is not manufactured or distributed by GSK Consumer Healthcare, Inc. the distributor of Gas-X® Extra strength.

Distributed by:

Pharmacy Value Alliance, LLC

407 East Lancaster Avenue,

Wayne, PA 19087

IMPORTANT: Keep this carton for future reference on full labeling.